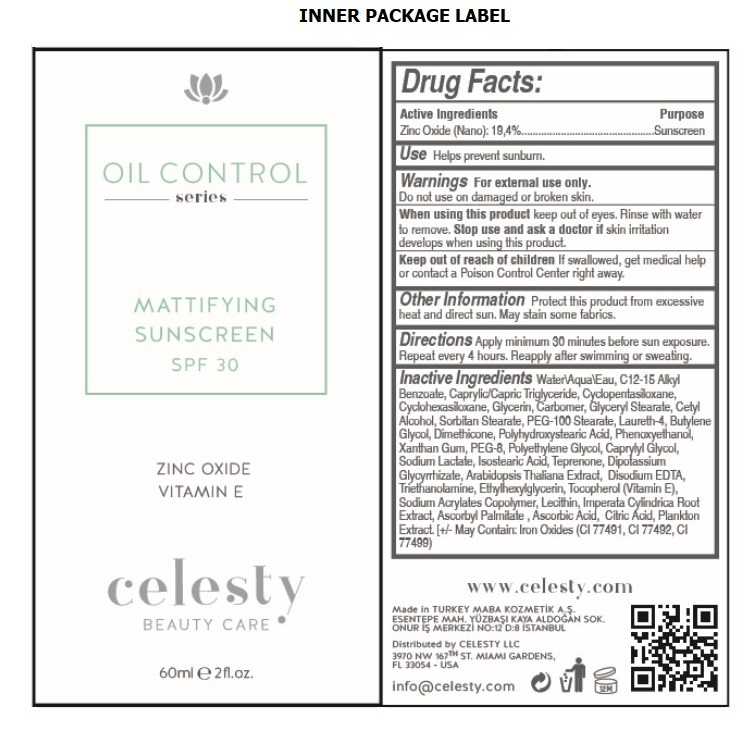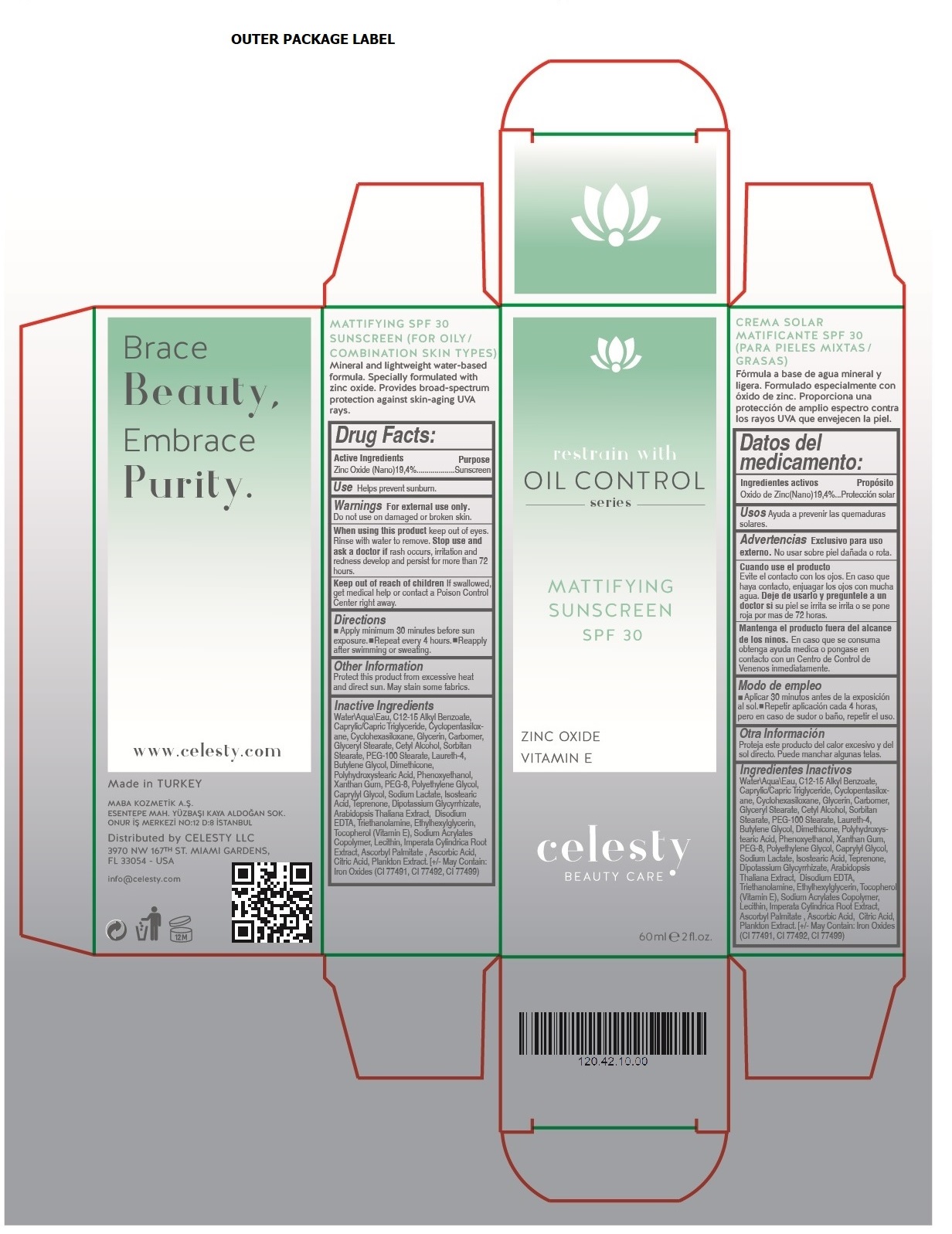 DRUG LABEL: Celesty
NDC: 81120-108 | Form: CREAM
Manufacturer: MABA KOZMETIK LIMITED SIRKETI
Category: otc | Type: HUMAN OTC DRUG LABEL
Date: 20201210

ACTIVE INGREDIENTS: ZINC OXIDE 194 mg/1 mL
INACTIVE INGREDIENTS: WATER; ALKYL (C12-15) BENZOATE; MEDIUM-CHAIN TRIGLYCERIDES; CYCLOMETHICONE 5; CYCLOMETHICONE 6; GLYCERIN; CARBOMER HOMOPOLYMER, UNSPECIFIED TYPE; GLYCERYL MONOSTEARATE; CETYL ALCOHOL; SORBITAN MONOSTEARATE; PEG-100 STEARATE; LAURETH-4; BUTYLENE GLYCOL; DIMETHICONE; POLYHYDROXYSTEARIC ACID (2300 MW); PHENOXYETHANOL; XANTHAN GUM; POLYETHYLENE GLYCOL 400; POLYETHYLENE GLYCOL, UNSPECIFIED; CAPRYLYL GLYCOL; SODIUM LACTATE; ISOSTEARIC ACID; TEPRENONE; GLYCYRRHIZINATE DIPOTASSIUM; ARABIDOPSIS THALIANA WHOLE; EDETATE DISODIUM ANHYDROUS; TROLAMINE; ETHYLHEXYLGLYCERIN; TOCOPHEROL; SODIUM POLYACRYLATE (2500000 MW); LECITHIN, SOYBEAN; IMPERATA CYLINDRICA ROOT; ASCORBYL PALMITATE; ASCORBIC ACID; CITRIC ACID MONOHYDRATE; DIATOMACEOUS EARTH; FERRIC OXIDE RED; FERRIC OXIDE YELLOW; FERROSOFERRIC OXIDE

Celesty OIL CONTROL Series MATTIFYING SUNSCREEN SPF 30

Active Ingredients

Zinc Oxide (Nano)19,4%

Purpose

Sunscreen

Use

Helps prevent sunburn.

Warnings

For external use only.

Do not use on damaged or broken skin.

When using this product keep out of eyes. Rinse with water to remove. Stop use and ask a doctor if rash occurs, irritation and redness develop and persist for more than 72 hours.

Keep out of reach of children If swallowed, get medical help or contact a Poison Control Center right away.

Directions

• Apply minimum 30 minutes before sun exposure. • Repeat every 4 hours. • Reapply after swimming or sweating.

Other Information

Protect this product from excessive heat and direct sun. May stain some fabrics.

Inactive Ingredients

Water\Aqua\Eau, C12-15 Alkyl Benzoate, Caprylic/Capric Triglyceride, Cyclopentasiloxane, Cyclohexasiloxane, Glycerin, Carbomer, Glyceryl Stearate, Cetyl Alcohol, Sorbitan Stearate, PEG-100 Stearate, Laureth-4, Butylene Glycol, Dimethicone, Polyhydroxystearic Acid, Phenoxyethanol, Xanthan Gum, PEG-8, Polyethylene Glycol, Caprylyl Glycol, Sodium Lactate, Isostearic Acid, Teprenone, Dipotassium Glycyrrhizate, Arabidopsis Thaliana Extract, Disodium EDTA, Triethanolamine, Ethylhexylglycerin, Tocopherol (Vitamin E), Sodium Acrylates Copolymer, Lecithin, Imperata Cylindrica Root Extract, Ascorbyl Palmitate, Ascorbic Acid, Citric Acid, Plankton Extract, [+/- May Contain: Iron Oxides (CI 77491, CI 77492, CI 77499)

restrain with OIL CONTROL series

ZINC OXIDE

VITAMIN E

BEAUTY CARE

(FOR OILY/COMBINATION SKIN TYPES)

Mineral and lightweight water-based formula. Specially formulated with zinc oxide. Provides broad-spectrum protection against skin-aging UVA rays.

Brace Beauty, Embrace Purity.

www.celesty.com

Made in TURKEY

MABA KOZMETIK A.S.

ESENTEPE MAH. YUZBASI KAYA ALDOGAN SOK.

ONUR IS MERKEZI NO:12 D:8 ISTANBUL

Distributed by CELESTY LLC

3970 NW 167TH ST. MIAMI GARDENS,

FL 33054 - USA

info@celesty.com